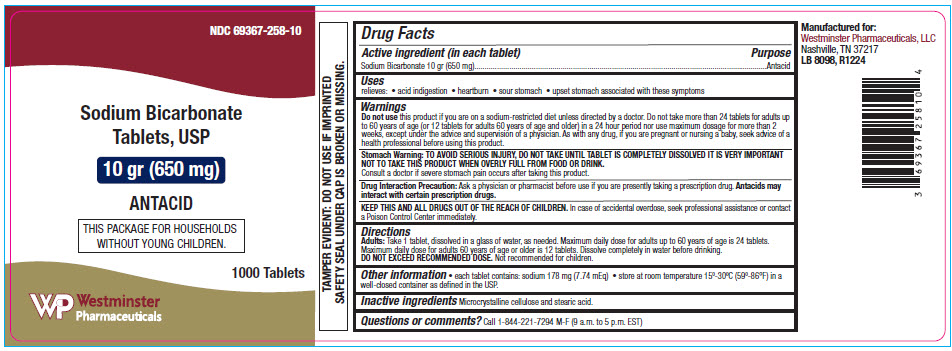 DRUG LABEL: Sodium Bicarbonate
NDC: 69367-258 | Form: TABLET
Manufacturer: Westminster Pharmaceuticals, LLC
Category: otc | Type: HUMAN OTC DRUG LABEL
Date: 20250708

ACTIVE INGREDIENTS: SODIUM BICARBONATE 650 mg/1 1
INACTIVE INGREDIENTS: MICROCRYSTALLINE CELLULOSE; STEARIC ACID

Sodium Bicarbonate

Drug Facts

Active ingredient (in each tablet)

Sodium Bicarbonate 10 gr (650 mg)

Purpose

Antacid

Uses

relieves

- acid indigestion
- heartburn
- sour stomach
- upset stomach associated with these symptoms

Warnings

Do not use this product if you are on a sodium-restricted diet unless directed by a doctor. Do not take more than 24 tablets for adults up to 60 years of age (or 12 tablets for adults 60 years of age and older) in a 24 hour period nor use maximum dosage for more than 2 weeks, except under the advice and supervision of a physician. As with any drug, if you are pregnant or nursing a baby, seek advice of a health professional before using this product.

Stomach Warning

TO AVOID SERIOUS INJURY, DO NOT TAKE UNTIL TABLET IS COMPLETELY DISSOLVED IT IS VERY IMPORTANT NOT TO TAKE THIS PRODUCT WHEN OVERLY FULL FROM FOOD OR DRINK.

Consult a doctor if severe stomach pain occurs after taking this product.

Drug Interaction Precaution

Ask a physician or pharmacist before use if you are presently taking a prescription drug. Antacids may interact with certain prescription drugs.

KEEP OUT OF REACH OF CHILDREN

KEEP THIS AND ALL DRUGS OUT OF THE REACH OF CHILDREN. In case of accidental overdose, seek professional assistance or contact a Poison Control Center immediately.

Directions

Adults

Take 1 tablet, dissolved in a glass of water, as needed. Maximum daily dose for adults up to 60 years of age is 24 tablets. Maximum daily dose for adults 60 years of age or older is 12 tablets. Dissolve completely in water before drinking.

DO NOT EXCEED RECOMMENDED DOSE. Not recommended for children.

Other information

- each tablet contains: sodium 178 mg (7.74 mEq)
- store at room temperature 15º-30ºC (59º-86°F) in a well-closed container as defined in the USP

Inactive ingredients

Microcrystalline cellulose and stearic acid

Questions or comments?

Call 1-844-221-7294 M-F (9 a.m. to 5 p.m. EST)

PRINCIPAL DISPLAY PANEL - 1000 Tablet Bottle Label

NDC 69367-258-10

Sodium Bicarbonate
Tablets, USP

10 gr (650 mg)

ANTACID

THIS PACKAGE FOR HOUSEHOLDS
WITHOUT YOUNG CHILDREN.

1000 Tablets

WP
Westminster
Pharmaceuticals